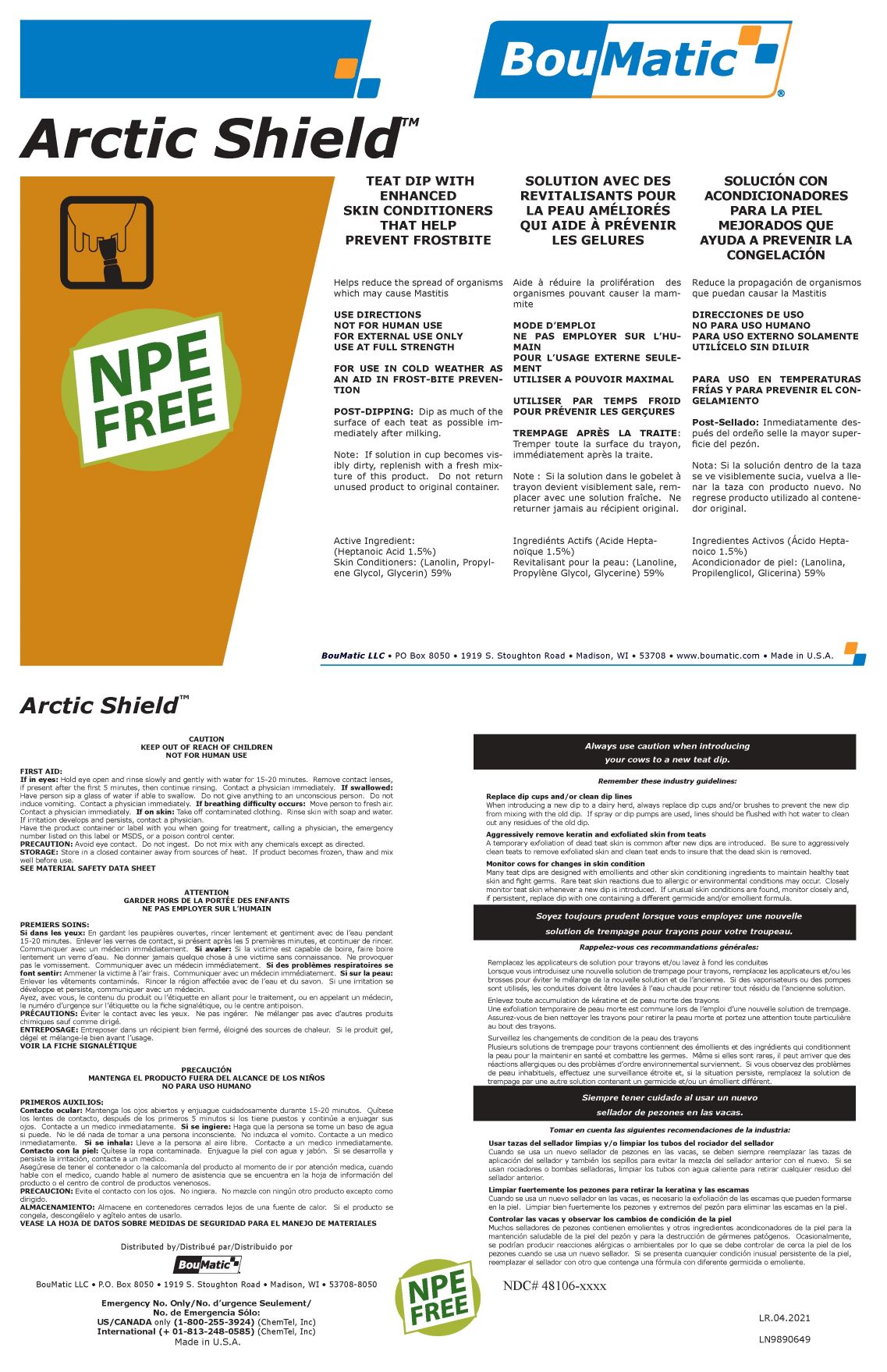 DRUG LABEL: ARCTIC SHIELD
NDC: 48106-2040 | Form: LIQUID
Manufacturer: BOUMATIC, LLC
Category: animal | Type: OTC ANIMAL DRUG LABEL
Date: 20210430

ACTIVE INGREDIENTS: HEPTANOIC ACID 1.5 g/100 g; PROPYLENE GLYCOL 29 g/100 g; GLYCERIN 20 g/100 g
INACTIVE INGREDIENTS: C8-10/PROPYLENE GLYCOL/PEG-22/DECYLENE GLYCOL ETHER 1.5 g/100 g; WATER 38 g/100 g; PEG-75 LANOLIN 10 g/100 g

Arctic Shield

USE DIRECTIONS

NOT FOR HUMAN USE
FOR EXTERNAL USE ONLY
USE AT FULL STRENGTH

FIRST AID:
If in eyes: Hold eye open and rinse slowly and gently with water for 15-20 minutes. Remove contact lenses,
if present after the first 5 minutes, then continue rinsing. Contact a physician immediately. If swallowed:
Have person sip a glass of water if able to swallow. Do not give anything to an unconscious person. Do not
induce vomiting. Contact a physician immediately. If breathing difficulty occurs: Move person to fresh air.
Contact a physician immediately. If on skin: Take off contaminated clothing. Rinse skin with soap and water.
If irritation develops and persists, contact a physician.
Have the product container or label with you when going for treatment, calling a physician, the emergency
number listed on this label or MSDS, or a poison control center.

Storage:

Store in a closed container away from sources of heat. If product becomes frozen, thaw and mix
well before use.

Post Dipping

Dip as much of the
surface of each teat as possible immediately
after milking.
Note: If solution in cup becomes visibly
dirty, replenish with a fresh mixture
of this product. Do not return
unused product to original container.

Arctic Shield label